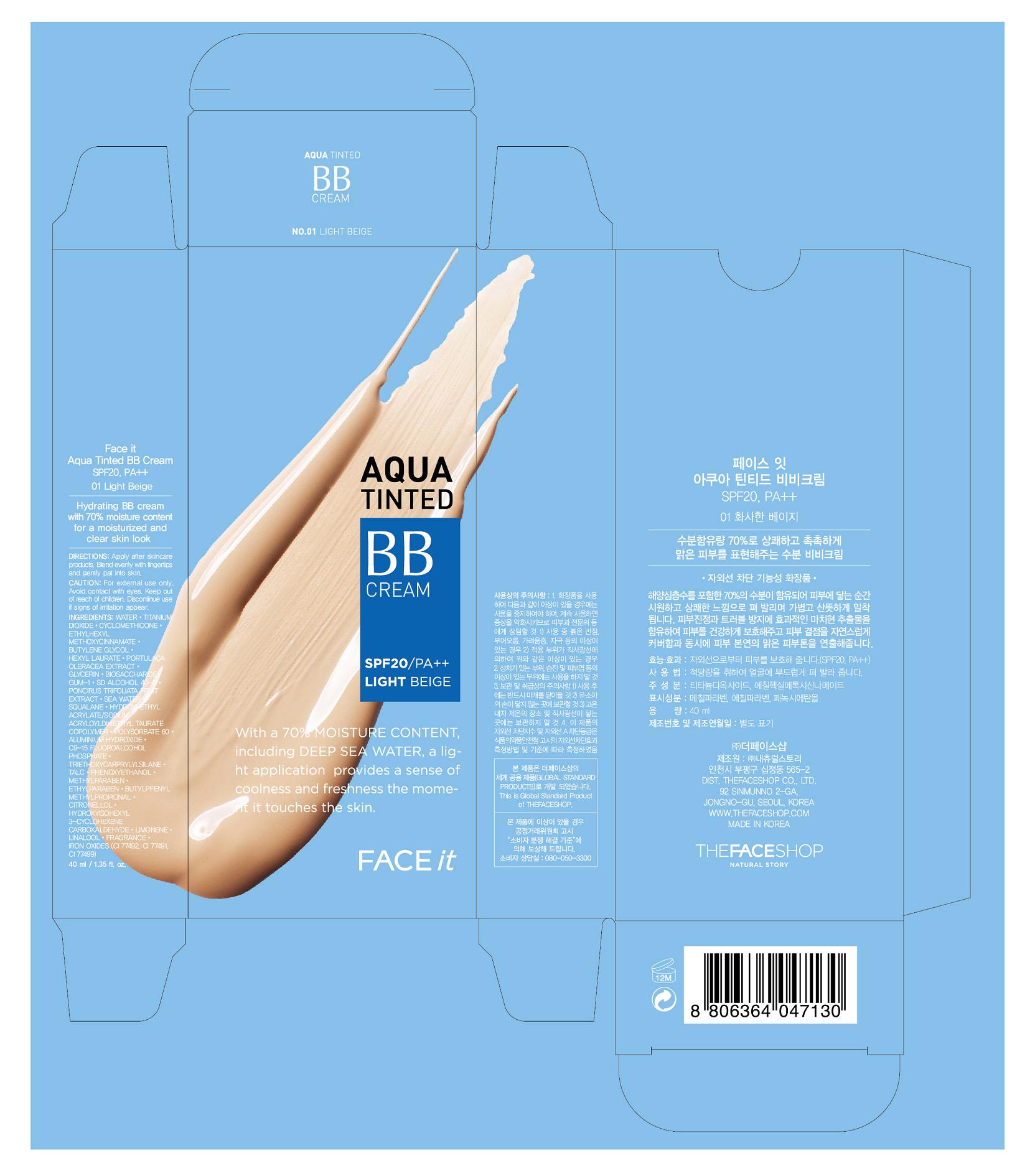 DRUG LABEL: FACE IT AQUA TINTED BB SPF 20 PA 01
NDC: 51523-105 | Form: CREAM
Manufacturer: THEFACESHOP CO., LTD
Category: otc | Type: HUMAN OTC DRUG LABEL
Date: 20110902

ACTIVE INGREDIENTS: TITANIUM DIOXIDE 5.80 mL/100 mL; OCTINOXATE 5 mL/100 mL
INACTIVE INGREDIENTS: WATER; CYCLOMETHICONE 5; BUTYLENE GLYCOL; HEXYL LAURATE; POLYSORBATE 60; SQUALANE; GLYCERIN; BIOSACCHARIDE GUM-1; PHENOXYETHANOL; FERRIC OXIDE YELLOW ; METHYLPARABEN; TALC; FERRIC OXIDE RED; ETHYLPARABEN; FERROSOFERRIC OXIDE; TRIETHOXYCAPRYLYLSILANE; BUTYLENE GLYCOL; PONCIRUS TRIFOLIATA FRUIT

Drug Facts

ACTIVE INGREDIENT

TITANIUM DIOXIDE (5.8%)
OCTINOXATE (5%)

INACTIVE INGREDIENT

WATER, CYCLOMETHICONE 5, BUTYLENE GLYCOL, HEXYL LAURATE, POLYSORBATE 60, SQUALANE, GLYCERIN, BIOSACCHARIDE GUM-1, PHENOXYETHANOL, FERRIC OXIDE YELLOW, METHYLPARABEN, TALC, FERRIC OXIDE RED, ETHYLPARABEN, FERROSOFERRIC OXIDE, TRIETHOXYCAPRYLYLSILANE, BUTYLENE GLYCOL, PONCIRUS TRIFOLIATA FRUIT

PURPOSE

Provides high protection against sunburn and tanning.

WHEN USING

Avoid contact with eyes.

STOP USE

Discontinue use if sign of irritation or rash appear.

DOSAGE AND ADMINISTRATION

Dispense an adequate amount and apply evenly. (At the final stage of basic skincare, dispense an adequate amount and apply evenly to desired parts)

PACKAGE LABEL

FACE IT AQUA TINTED BB SPF 20 PA 01